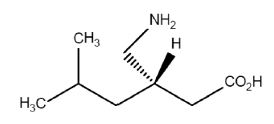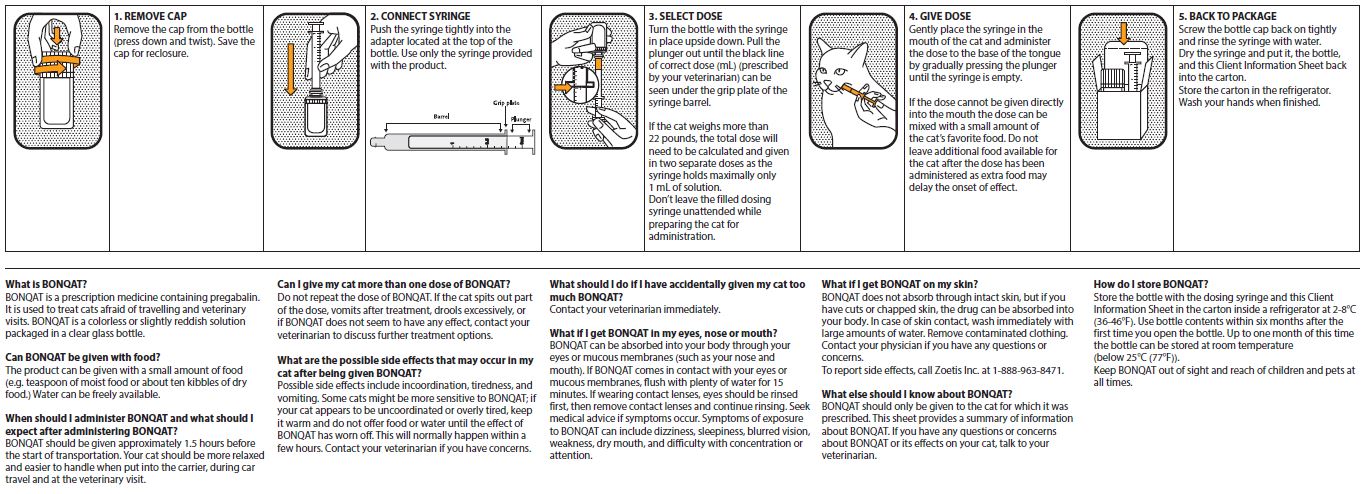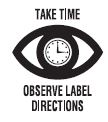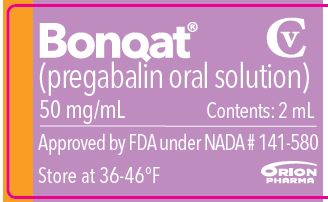 DRUG LABEL: BONQAT
NDC: 54771-1906 | Form: SOLUTION
Manufacturer: Zoetis Inc.
Category: animal | Type: PRESCRIPTION ANIMAL DRUG LABEL
Date: 20240327
DEA Schedule: CV

ACTIVE INGREDIENTS: PREGABALIN 50 mg/1 mL

Bonqat®

Bonqat® CV
(pregabalin oral solution)
Each mL of BONQAT contains 50 mg pregabalin.
For oral use in cats only.
CAUTION:
Federal law restricts this drug to use by or on the order of a licensed veterinarian.

DESCRIPTION

Each mL of BONQAT contains 50 mg pregabalin. The chemical name of pregabalin is (3S)-3-(aminomethyl)-5-methylhexanoic acid. It is a white or almost white powder having a molecular weight of 159.23g /mol. The molecular formula is C8H17NO2 and the structural formula is:

INDICATIONS

BONQAT is indicated for alleviation of acute anxiety and fear associated with transportation and veterinary visits in cats.

DOSAGE AND ADMINISTRATION

Client Information Sheet is on the reverse of this package insert.
Always provide client information sheet with prescription.
BONQAT is administered orally as a single dose of 5 mg/kg (0.1 mL/kg) approximately 1.5 hours before the start of the transportation or veterinary visit and can be given on two consecutive days.
If the cat weighs more than 22 pounds, the total dose will need to be calculated and given in two separate doses as the syringe holds a maximum of 1 mL of solution.
A small amount of food can be given with BONQAT.

CONTRAINDICATIONS

Do not use in case of hypersensitivity to pregabalin or to any of the excipients (sodium benzoate, ethyl maltol, hydrochloric acid, sodium hydroxide).

WARNINGS

Human Safety Warnings:
Not for human use.

Appropriate precautions should be taken while handling BONQAT. Avoid skin contact, eye contact, or contact with mucous membranes.
Symptoms of exposure to pregabalin include dizziness, sleepiness, blurred vision, weakness, dry mouth, and difficulty with concentration or attention.
In case of accidental eye or mucosal exposure, flush with water for 15 minutes. If wearing contact lenses, eyes should be rinsed first, then remove contact lenses and continue rinsing. Seek medical advice if symptoms occur.
In case of skin contact, wash with soap and water immediately. Remove contaminated clothing. Seek medical advice if symptoms occur.
In case of accidental ingestion, seek medical advice if symptoms occur. Do not drive as sleepiness may occur. In case of ingestion by a child, seek medical attention immediately. Show the package insert or the label to the physician.
Drug Abuse, Addiction, and Diversion
Controlled Substance:
BONQAT contains pregabalin, a Schedule V controlled substance.
Abuse: Abuse is defined as the intentional, non-therapeutic use of a drug, even once, to achieve a desired psychological or physiological effect. Pregabalin is not known to be active at receptor sites associated with drugs of abuse. However, pregabalin is associated with drug liking and is known to be misused and abused in the community, particularly in combination with opioids. Consider the potential risks of misuse or abuse before prescribing this product. Signs of pregabalin misuse or abuse include drug seeking behavior.
Pregabalin should be handled appropriately to minimize the risk of diversion, including restriction of access, the use of accounting procedures, and proper disposal methods, as appropriate to the clinical setting and as required by law.
Note to physician: BONQAT contains pregabalin.
The safety data sheet (SDS) contains more detailed occupational safety information. To report adverse reactions in users or to obtain a copy of the SDS for BONQAT contact Zoetis Inc. at 1-888-963-8471.
Animal Safety Warnings: Some cats may experience hypothermia, depression, drowsiness, muscle tremors, and/or ataxia. These cats should be kept warm and not offered food or water until BONQAT’s effects have worn off (usually within 6 hours). (See TARGET ANIMAL SAFETY)
Keep BONQAT in a secure location out of reach of dogs, cats, and other animals to prevent accidental ingestion or overdose.

PRECAUTIONS

Use with caution in cats with concurrent cardiac disease or hypertension because BONQAT may cause bradycardia and reflex hypertension. The safety of BONQAT has not been evaluated in cats with concurrent cardiac disease or hypertension.

The safe use of BONQAT in cats younger than 7 months of age has not been evaluated.

The safe use of BONQAT used in conjunction with opioids and other sedatives has not been evaluated.

Use with caution in cats with pre-existing renal disease (See Clinical Pharmacology).

The safe use of BONQAT in cats with severe systemic disorders has not been evaluated. Use with caution in cats with severe systemic disorder.

The safe use of BONQAT in breeding, pregnant, and lactating cats has not been evaluated.

ADVERSE REACTIONS

In a well-controlled European field study, which included a total of 238 cats (108 treated with BONQAT at the label dose of 5 mg/kg, 29 treated with BONQAT at a dose of 2.5 mg/kg, and 101 administered placebo control), 5 months to 15 years of age and weighing 1.8 to 10.3 kg, the following adverse reactions were reported:
Table 1. Adverse reactions

Adverse reaction | Pregabalin 5 mg/kg N=108 | Pregabalin 2.5 mg/kg N=29 | Placebo N=101
Ataxia | 5 (4.6%) | 1 (3.4%) | 0
Lethargy | 3 (2.8%) | 2 (6.9%) | 0
Emesis | 2 (1.9%) | 0 | 0
Proprioception abnormality | 1 (0.9%) | 1 (3.4%) | 0
Muscle tremor | 1 (0.9%) | 0 | 0
Anorexia | 1 (0.9%) | 0 | 0
Weight loss | 1 (0.9%) | 0 | 0
Mydriasis | 0 | 1 (3.4%) | 0

CONTACT INFORMATION

To report suspected adverse events, for technical assistance or to obtain a copy of the SDS, contact Zoetis Inc. at 1-888-963-8471.
For additional information about adverse drug experience reporting for animal drugs, contact FDA at 1-888-FDA-VETS or online at www.fda.gov/reportanimalae.

INFORMATION FOR CAT OWNERS

Possible side effects on BONQAT include incoordination, tiredness, and vomiting. Some cats might be more sensitive to BONQAT; if the cat appears to be uncoordinated or overly tired, it should be kept warm and not offered food or water until the effect of BONQAT has worn off. This will normally happen within a few hours. If there are further concerns related to side effects after dosing the veterinarian should be contacted.
BONQAT must not be re-dosed if the cat spits part of the dose, vomits after treatment, or in case of hypersalivation, or if BONQAT does not seem to have any effect.
Always provide the Client Information Sheet with prescription.
Keep BONQAT in a secure location out of reach of children, dogs, cats, and other animals to prevent accidental ingestion or overdose.

CLINICAL PHARMACOLOGY

Absorption
BONQAT is rapidly absorbed after oral administration in cats. Following oral administration of 5 mg/kg to fasted cats the maximum observed concentration (Cmax) in plasma was 10.1 ± 0.8 (SD) μg/mL and occurred at 0.5-1.0 hours post-dose. The area under plasma concentration time curve from time zero to the last quantifiable time point (AUClast) was 199±27 μg*h/mL. The mean absolute oral bioavailability was 94.3%.
Distribution
BONQAT has a relatively large volume of distribution. After intravenous (IV) bolus administration of 2.5 mg/kg, the volume of distribution at the steady state (Vss) was 0.4±0.02 L/kg in cats. BONQAT is not known to bind to plasma proteins in other species, but this has not been studied in cats.
Metabolism and excretion
BONQAT is slowly eliminated from the body of cats. After IV bolus administration of 2.5 mg/kg, total plasma clearance was 0.03±0.008 L/h/kg. The mean half-life of elimination from circulation was 12.3±3.1 hours after IV administration of 2.5 mg/kg and 14.7±2.7 hours after oral administration of 5 mg/kg.

Elimination of the parent compound as well as the methylation metabolite from circulation occurs almost exclusively by renal excretion in other species. This has not been studied in cats.
Mechanism of Action
Pregabalin is a ligand of alpha2-delta subunit of voltage-gated calcium channels. It reduces the presynaptic calcium influx in neurons and thereby the release of various neurotransmitters, including glutamate, norepinephrine, serotonin, dopamine, substance P and calcitonin gene-related peptide.

EFFECTIVENESS

The effectiveness of BONQAT was demonstrated in a well-controlled multi-center field study conducted in Europe. A total of 238 cats with a history of being anxious and/or fearful when transported by a car and during veterinary visits were allocated to 1 of 3 treatment groups: 108 cats received BONQAT orally at a dose of 5 mg/kg, 29 cats received BONQAT at a dose of 2.5 mg/kg and 101 cats received placebo (vehicle oral solution containing no active ingredient). The study included assessments during transportation and veterinary examination at a screening visit and a treatment visit. To keep both study visits as similar as possible, all cats were administered tap water prior to the screening visit. Prior to the treatment visit, each cat was administered its randomized treatment. The treatment visit was conducted 5-10 days after the screening visit in a similar manner as the screening visit. Doses were administered approximately 1.5 hours before the cat was put into the carrier and starting of the transportation to the visits. The cats were between 5 months and 15 years of age and weighed 1.8 to 10.3 kg.
Treatment success was defined with 2 primary effectiveness endpoints: the owner’s assessment of the treatment effect based on the cat’s anxiety and/or fear during transportation in a car and the veterinarian’s assessment of the treatment effect based on the cat’s anxiety and/or fear during physical examination at the clinic. These endpoints were based on the following scale (1- Excellent, 2- Good, 3- Fair, 4- Poor, 5- Very Poor).
The treatment effect was statistically significant for both primary effectiveness variables (p < 0.0010) in the group administered BONQAT at the dose 5 mg/kg compared to the placebo group. In the 5 mg/kg group, cat owners assessed the response as excellent or good during the transportation in 54.3% of cases; the corresponding proportion in the placebo group was 27.1%. In the 5 mg/kg group, the veterinarians assessed the response as excellent or good during the clinical examination in 52% of cases; the corresponding proportion in the placebo group was 30%. The 2.5 mg/kg group was not statistically different than placebo for both primary variables.
The owner’s assessment of ability to place the cat into the carrier was improved from screening to treatment visit in the group administered BONQAT at the dose of 5 mg/kg compared to the placebo group. The owner-assessed signs of anxiety and/or fear decreased from screening to treatment visit in the 5 mg/kg group compared to the placebo group . Based on the owners’ observations, vocalization, panting/intense breathing, activity, resistance, and freezing were the signs with the greatest improvement between screening and treatment visits in the 5 mg/kg group. The majority of the cat owners assessed administration of BONQAT as either very easy or easy.

TARGET ANIMAL SAFETY

In a margin of safety study, 32 healthy, 7-month-old Domestic shorthair cats (4/sex/group) were administered a negative control or BONQAT for six consecutive days by once daily oral administration at dose levels of 5, 15, and 25 mg/kg/day.
At 5 mg/kg/day, observed signs of sedation included: abnormal gait, slight to moderate uncoordinated behavior, decreased activity, slightly limited usage of hind limbs, lying on side, hypothermia and/or drowsy appearance (i.e. depression, drowsiness, and/or ataxia). Clinical signs of sedation were resolved at the four-hour clinical observation. One male and one female cat had hypothermia observed two to four hours post-dose respectively, the lowest body temperature value was 99°F. Cats had a decrease in heart rate with maximum effect at six hours, but the heart rates stayed within normal range. All adverse observations were resolved by six hours after dosing on the first day of treatment.
At 15 and 25 mg/kg/day, signs of sedation were observed in all cats and included ataxia, lethargy, slightly to moderately limited usage of hind limbs, slight to severe uncoordinated behavior, partially to completely closed eyes, lying on side, dilated pupils, hypothermia, and/or drowsy appearance (i.e. depression, drowsiness, and/or ataxia). On Day 1, all cats had a decreased body temperature at one or more timepoints, the lowest values were 97.8°F when dosed at 15 mg/kg/day and 98.2°F when dosed at 25 mg/kg/day. One cat dosed at 25 mg/kg/day had a loss of consciousness, abnormal gait, eyes closed, decreased activity, lying on side, sedation, salivation, vomiting, hypothermia, and uncoordinated behavior. This cat recovered by the four-hour observation. Directly after dosing, slight to severe salivation was observed in multiple cats on one or more days. Cats had decreased heart rate with maximum effect at two to six hours, some cats had bradycardia (120-130 bpm). The majority of cats maintained a normal blood pressure, but a few cats with bradycardia had a reflexive hypertension. Most adverse observations resolved by eight hours after treatment administration.
In a second margin of safety study, 32 healthy, 1 to 3 years old Domestic shorthair cats (4/sex/group) were administered a negative control or BONQAT for 3 consecutive days by once daily oral administration at dose levels of 5, 15 and 25 mg/kg/day. Directly after dosing, slight to severe hypersalivation was noted in all dose groups.
At 5 mg/kg/day, signs of sedation were observed in 6 of 8 cats, and included: abnormal gait, hypothermia, decreased respiratory rate and/or lethargy. These signs were observed between 1 and 6 hours after dosing on the first day of treatment. On Day 2, at six hours post-dose, one cat had muscle tremors that resolved without treatment by the 8-hour observation. Three cats had bradycardia (120-128 bpm) with maximum effect from two to six hours post-dose, but the heart rate remained within the normal range for the other five cats.
At 15 and 25 mg/kg/day, signs of sedation observed in all cats included: ataxia, hypothermia, lethargy, uncoordinated behavior, decreased respiratory rate, and/or they were cold to the touch. The signs of sedation were observed for 12 hours after dosing. One cat in the 15 mg/kg/day dose group had muscle tremors at four hours post-dosing as well as ataxia, lethargy, hypothermia, and a decrease in heart rate. Cats had a decrease in heart rate with maximum effect at two to six hours, a few cats had bradycardia (106-122 bpm). The majority of cats maintained a normal blood pressure, but a few cats with bradycardia had a reflex hypertension. One cat in the 15 mg/kg/day dose group had bradycardia with reflex hypertension at two hours post-dose followed by a reflex tachycardia at six- and eight-hours post-dose.

STORAGE INFORMATION

Store the bottle in a refrigerator at 2-8°C (36-46°F). Use bottle contents within six months after the first opening of the bottle. Up to one month of this time the bottle can be stored at or below 25°C (77°F).

HOW SUPPLIED

BONQAT is packed in a clear 5 mL glass bottle containing 2 mL of BONQAT (pregabalin oral solution) at 50 mg/mL. The bottle has a child resistant closure and an oral dosing syringe adapter. The bottle is further packed into a carton with a package insert and an oral dosing syringe (1 mL).

INFORMATION SHEET

Bonqat® CV
(pregabalin oral solution)

CLIENT INFORMATION SHEET FOR OWNER/HANDLER USE AND SAFETY
This sheet summarizes the basic information about BONQAT and does not replace the instructions from your veterinarian.
Talk to your veterinarian if you have questions regarding any part of this information or if you want to know more about BONQAT.

INSTRUCTIONS FOR USE

Orion Pharma
Zoetis

Approved by FDA under NADA # 141-580
BONQAT® is a trademark of Orion Corporation.
Manufactured by:
Orion Corporation
Turku, Finland
Distributed by:
Zoetis Inc.
Kalamazoo, MI 49007
Issued: November 2023

PRINCIPAL DISPLAY PANEL

160463